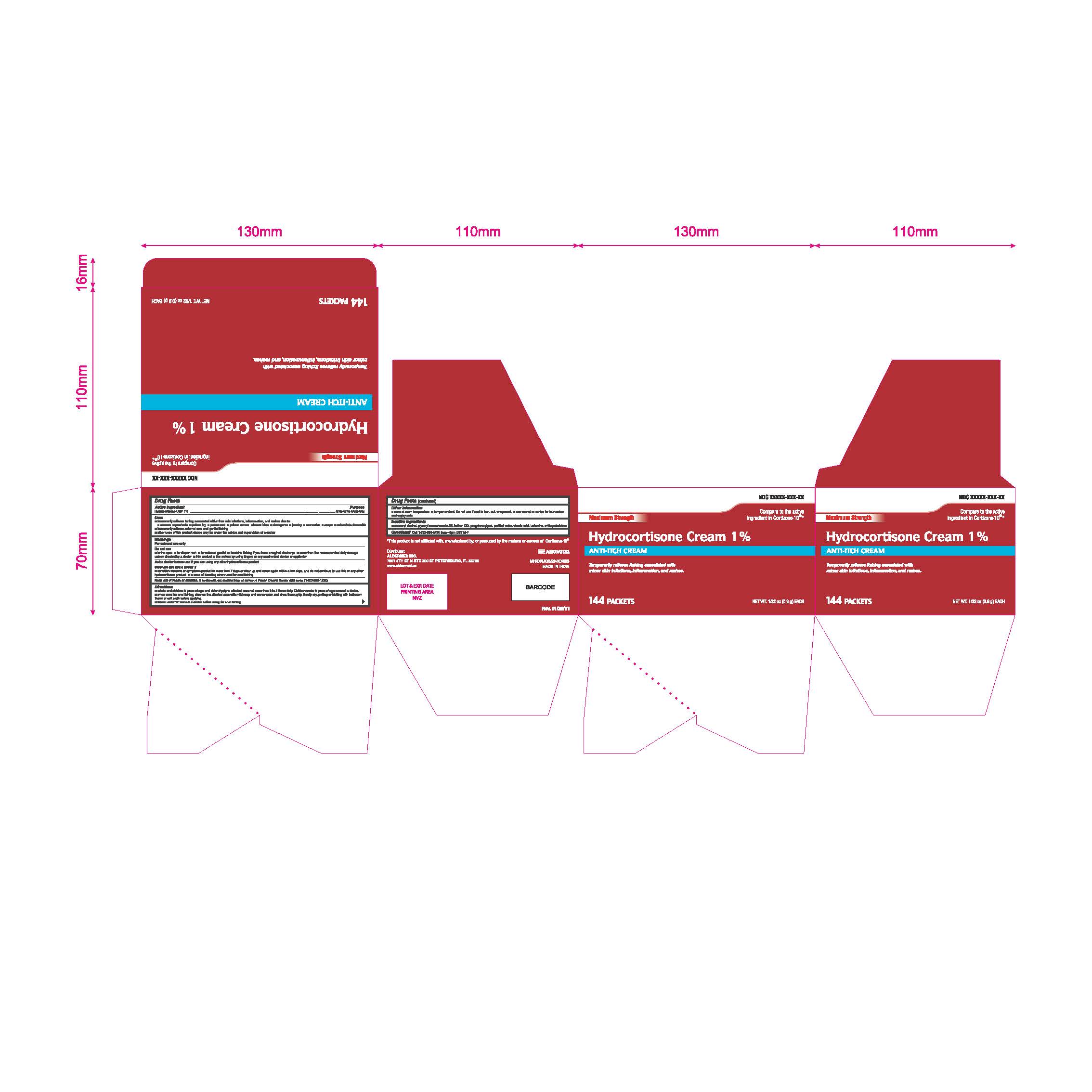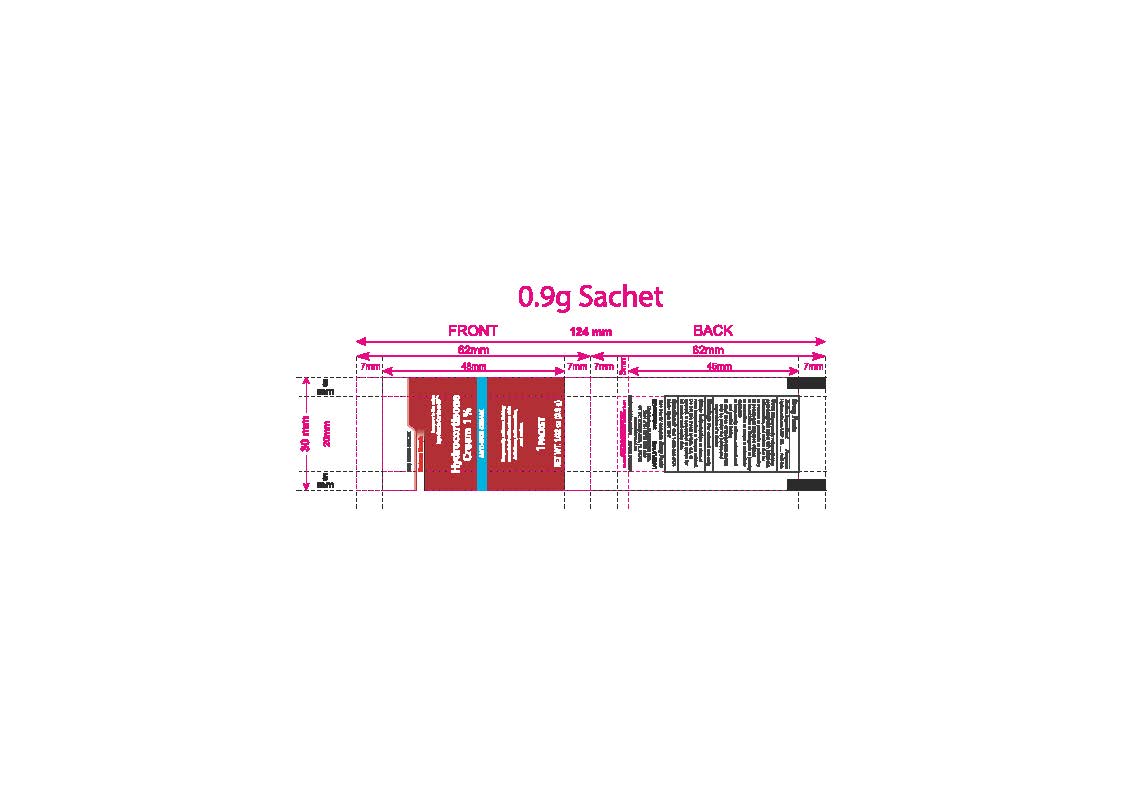 DRUG LABEL: Hydrocortisone
NDC: 87236-004 | Form: CREAM
Manufacturer: Aldermed Inc.
Category: otc | Type: HUMAN OTC DRUG LABEL
Date: 20260210

ACTIVE INGREDIENTS: HYDROCORTISONE 1 g/100 g
INACTIVE INGREDIENTS: WHITE PETROLATUM; TROLAMINE; STEARIC ACID; PROPYLENE GLYCOL; CETOSTEARYL ALCOHOL; METHYLCHLOROISOTHIAZOLINONE/METHYLISOTHIAZOLINONE MIXTURE; GLYCERYL MONOSTEARATE; WATER

Hydrocortisone Cream 1%

Drug Facts

Active ingredient

Hydrocortisone USP 1%

Purpose

Antipruritic (Anti-itch)

Uses

- temporarily relieves itching associated with minor skin irritations, inflammation, and rashes due to
  - eczema
  - psoriasis
  - poison ivy
  - poison oak
  - poison sumac
  - insect bites
  - detergents
  - jewelry
  - cosmetics
  - soaps
  - seborrheic dermatitis
- temporarily relieves external anal and genital itching
- other uses of this product should be only under the advice and supervision of a doctor

Warnings

For external use only

Do not use

- in the eyes
- for diaper rash
- for genital or feminine itching if you have a vaginal discharge.
- more than the recommended daily dosage unless directed by a doctor.
- this product in the rectum by using fingers or any mechanical device or applicator.

Ask a doctor before use if you are

using any other hydrocortisone product

Stop use and ask a doctor if

- condition worsens, symptoms persist for more than 7 days or clear up and occur again within a few days, and do not continued to use this or any other hydrocortisone product
- in case of bleeding when used for anal itchingoccurs

Keep out of reach of children

If swallowed, get medical help or contact a Poison Control Center right away. (1-800-222-1222)

Directions

- adults and children 2 years of age and older: apply to affected area not more than 3 to 4 times daily
- children under 2 years of age: ask a doctor

- when used for anal itching, cleanse the affected area with mild soap and warm water and rinse thoroughly. Gently dry, patting or blotting with bathroom tissue or soft cloth before applying.
- children under 12: consult a doctor before using for anal itching.

Other information

- store at room temperature
- tamper evident. Do not use if seal is torn, cut, or opened.
- see sachet or carton for lot numebr and expiry date

Inactive ingredients

Cetostearyl Alcohol, Glyceryl Monostearate SE, Kathon CG, Propylene Glycol, Purified Water, Stearic Acid, Trolamine, White Petrolatum

Questions or Comments?

Call 1-833-605-8474 9am-5pm EST M-F